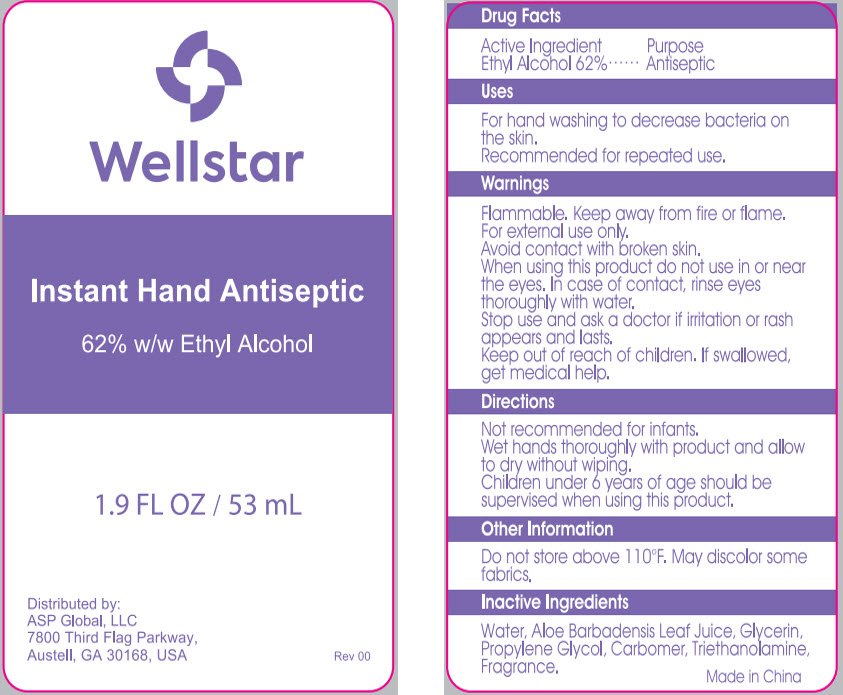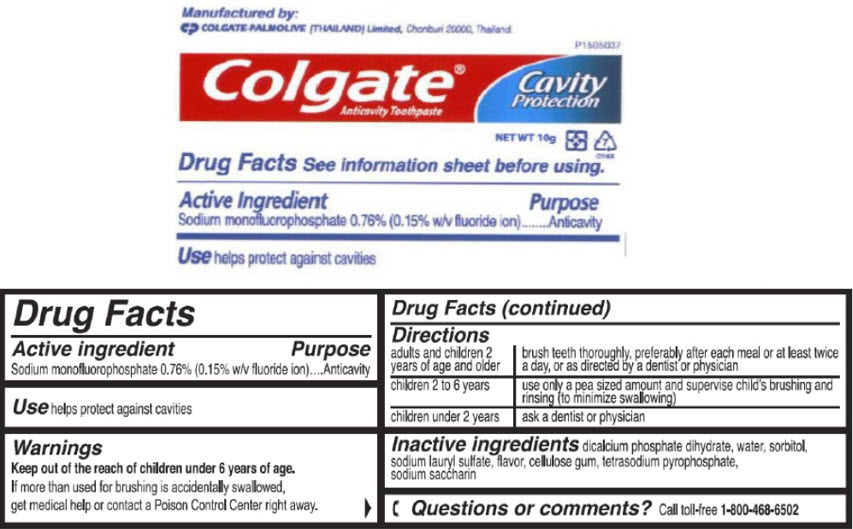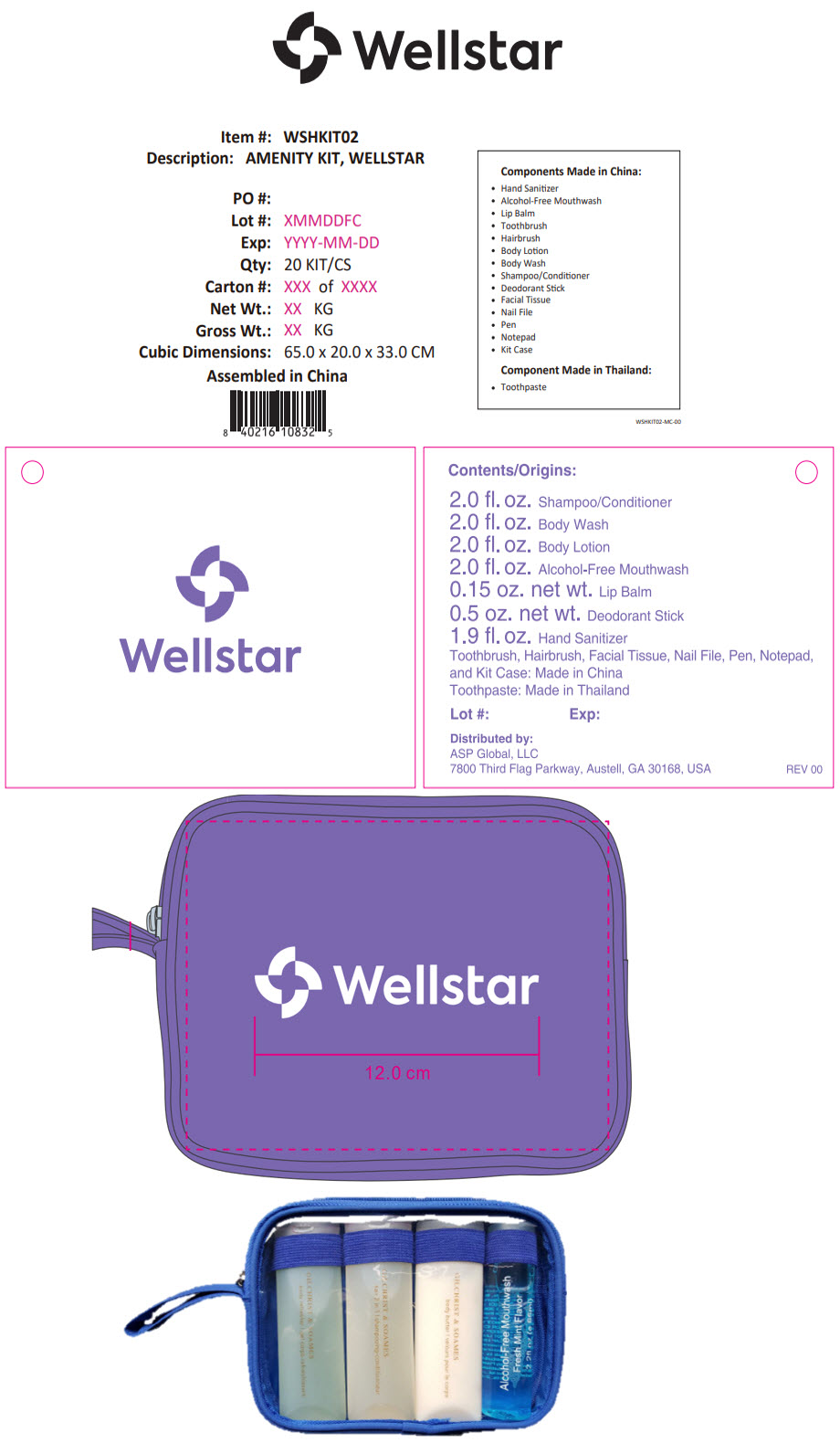 DRUG LABEL: Wellstar Amenity
NDC: 59448-800 | Form: KIT | Route: TOPICAL
Manufacturer: ASP Global, LLc
Category: otc | Type: HUMAN OTC DRUG LABEL
Date: 20241217

ACTIVE INGREDIENTS: Alcohol 62 mL/100 mL; Sodium Monofluorophosphate 7.6 mg/1 g
INACTIVE INGREDIENTS: Water; Aloe Vera Leaf; Glycerin; Propylene Glycol; CARBOMER INTERPOLYMER TYPE A (ALLYL SUCROSE CROSSLINKED); Trolamine; Dibasic Calcium Phosphate Dihydrate; Water; Sorbitol; Sodium Lauryl Sulfate; Sodium Pyrophosphate; Saccharin Sodium

Wellstar Amenity Kit

Instant Hand Antiseptic

Drug Facts

Active Ingredient

Ethyl Alcohol 62%

Purpose

Antiseptic

Uses

For hand washing to decrease bacteria on the skin.

Recommended for repeated use.

Warnings

Flammable. Keep away from fire or flame.

For external use only.

Avoid contact with broken skin.

When using this product do not use in or near the eyes. In case of contact, rinse eyes thoroughly with water.

Stop use and ask a doctor if irritation or rash appears and lasts.

Keep out of reach of children. If swallowed, get medical help.

Directions

Not recommended for infants.

Wet hands thoroughly with product and allow to dry without wiping.

Children under 6 years of age should be supervised when using this product.

Other Information

Do not store above 110°F. May discolor some fabrics.

Inactive Ingredients

Water, Aloe Barbadensis Leaf Juice, Glycerin, Propylene Glycol, Carbomer, Triethanolamine, Fragrance.

Distributed by:
ASP Global, LLC
7800 Third Flag Parkway,
Austell, GA 30168, USA

Colgate® Anticavity Toothpaste

Drug Facts

Active ingredient

Sodium monofluorophosphate 0.76% (0.15% w/v fluoride ion)

Purpose

Anticavity

Use

helps protect against cavities

Warnings

KEEP OUT OF REACH OF CHILDREN

Keep out of the reach of children under 6 years of age.

If more than used for brushing is accidentally swallowed, get medical help or contact a Poison Control Center right away.

Directions

adults and children 2 years of age and older | brush teeth thoroughly, preferably after each meal or at least twice a day, or as directed by a dentist or physician
children 2 to 6 years | use only a pea sized amount and supervise child's brushing and rinsing (to minimize swallowing)
children under 2 years | ask a dentist or physician

Inactive ingredients

dicalcium phosphate dihydrate, water, sorbitol, sodium lauryl sulfate, flavor, cellulose gum, tetrasodium pyrophosphate, sodium saccharin

Questions or comments?

Call toll-free 1-800-468-6502

Manufactured by:
COLGATE-PALMOLIVE (THAILAND) Limited, Chonburi 20000, Thailand.

PRINCIPAL DISPLAY PANEL - 53 mL Bottle Label

Wellstar

Instant Hand Antiseptic

62% w/w Ethyl Alcohol

1.9 FL OZ / 53 mL

Distributed by:
ASP Global, LLC
7800 Third Flag Parkway,
Austell, GA 30168, USA

Rev 00

PRINCIPAL DISPLAY PANEL - 10 g Tube Label

P1505037

Colgate®
Anticavity Toothpaste

Cavity
Protection

NET WT 10g

7
OTHER

PRINCIPAL DISPLAY PANEL - Kit Label

Wellstar

Item #: WSHKIT02
Description: AMENITY KIT, WELLSTAR
PO #:
Lot #: XMMDDFC
Exp: YYYY-MM-DD
Qty: 20 KIT/CS
Carton #: XXX of XXXX
Net Wt.: XX KG
Gross Wt.: XX KG
Cubic Dimensions: 65.0 x 20.0 x 33.0 CM

Assembled in China

Components Made in China:

- Hand Sanitizer
- Alcohol-Free Mouthwash
- Lip Balm
- Toothbrush
- Hairbrush
- Body Lotion
- Body Wash
- Shampoo/Conditioner
- Deodorant Stick
- Facial Tissue
- Nail File
- Pen
- Notepad
- Kit Case

Component Made in Thailand:

- Toothpaste

WSHKIT02-MC-00

Wellstar

Contents/Origins:

2.0 fl. oz. Shampoo/Conditioner
2.0 fl. oz. Body Wash
2.0 fl. oz. Body Lotion
2.0 fl. oz. Alcohol-Free Mouthwash
0.15 oz. net wt. Lip Balm
0.5 oz. net wt. Deodorant Stick
1.9 fl. oz. Hand Sanitizer

Toothbrush, Hairbrush, Facial Tissue, Nail File, Pen, Notepad,
and Kit Case: Made in China
Toothpaste: Made in Thailand

Lot #:
Exp:

Distributed by:
ASP Global, LLC
7800 Third Flag Parkway, Austell, GA 30168, USA

REV 00

Wellstar